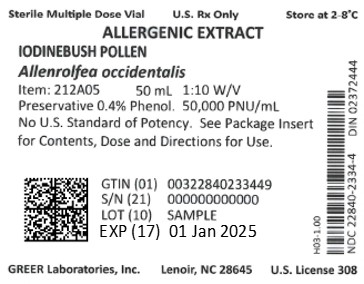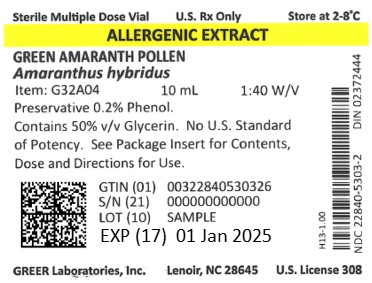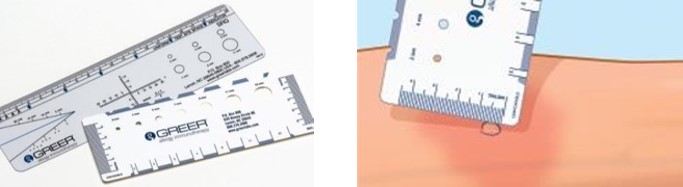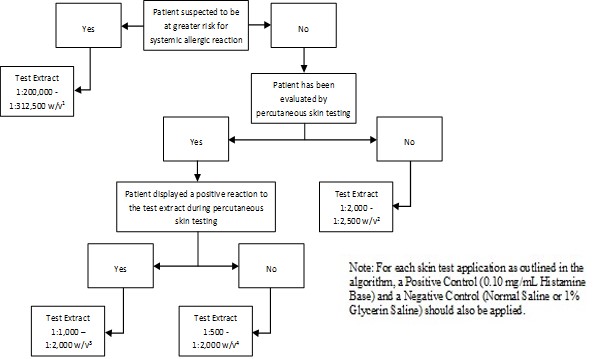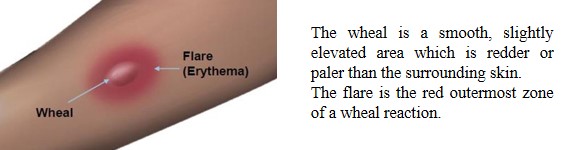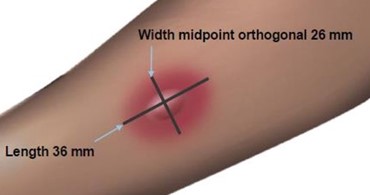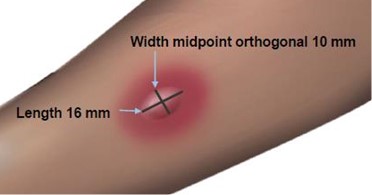 DRUG LABEL: Dog Fennel
NDC: 22840-5306 | Form: SOLUTION
Manufacturer: Greer Laboratories, Inc.
Category: other | Type: NON-STANDARDIZED ALLERGENIC LABEL
Date: 20250603

ACTIVE INGREDIENTS: EUPATORIUM CAPILLIFOLIUM POLLEN 0.0125 g/1 mL
INACTIVE INGREDIENTS: SODIUM BICARBONATE; PHENOL; SODIUM CHLORIDE

Non Standardized Allergenic Extracts
Pollens, Molds, Epidermals, Insects, Dusts, Foods, and Miscellaneous Inhalants

RECENT MAJOR CHANGES

Warning and Precautions, Anaphylaxis Following False Negative Food Allergen Skin Test Results (5.3) 01/2023

HIGHLIGHTS OF PRESCRIBING INFORMATION

These highlights do not include all the information needed to use Non-Standardized Allergenic Extracts (Pollens, Molds, Epidermals, Insects, Foods and Miscellaneous Inhalants) safely and effectively. See full prescribing information for Non-Standardized Allergenic Extracts.

Non-Standardized Allergenic Extracts (Pollens, Molds, Epidermals, Insects, Foods, and Miscellaneous Inhalants)

Solutions for percutaneous, intradermal or subcutaneous administration.

Initial U.S. Approval: 1968

WARNING: SEVERE ALLERGIC REACTIONS

See full prescribing information for complete boxed warning.

- Non-Standardized Allergenic Extracts can cause severe life-threatening systemic reactions, including anaphylaxis. (5.1)
- Do not administer these products to patients with severe, unstable or uncontrolled asthma. (4)
- Observe patients in the office for at least 30 minutes following treatment.Emergency measures and personnel trained in their use must be available immediately in the event of a life-threatening reaction. (5.1)
- Patients with extreme sensitivity to these products, on an accelerated immunotherapy build-up, switching to another lot, receiving high doses of these products, and patients exposed to similar allergens may be at increased risk of a severe allergic reaction. (5.1)
- These products may not be suitable for patients with certain underlying medical conditions that may reduce their ability to survive a systemic allergic reaction, and for patients receiving medications such as beta-blockers that may make them unresponsive to epinephrine or inhaled bronchodilators. (5.1, 5.2)

RECENT MAJOR CHANGES
Warning and Precautions, Anaphylaxis Following False Negative Food Allergen Skin Test Results (5.3) 01/2023

INDICATIONS AND USAGE

Non-Standardized Allergenic Extracts are indicated for:

- Skin test diagnosis of patients with a clinical history of allergies to one or more of the specific allergens. (1)
- Immunotherapy for reduction of allergen-induced allergic symptoms confirmed by appropriate positive skin tests or in vitro testing for allergen-specific IgE antibodies. (1)

Food extracts have not been proven safe or effective in allergen immunotherapy.

DOSAGE AND ADMINISTRATION

For percutaneous, intradermal or subcutaneous use only.

The extracts are diluted with sterile diluents when used for intradermal testing or subcutaneous immunotherapy. For percutaneous testing, the extracts are diluted with sterile diluents in patients expected to be at greater risk for systemic allergic reaction. Dosages vary by mode of administration and by individual response. See full prescribing information for instructions on preparation, administration, and adjustments of dose. (2.1)

DOSAGE FORMS AND STRENGTHS

Non-Standardized Allergenic Extracts are labeled in weight/volume and/or protein nitrogen units (PNU)/milliliter (a measure of total protein), and are supplied as sterile aqueous stock concentrates at up to 1:10 weight/volume or 40,000 PNU/milliliter, or 50% glycerin stock concentrates at up to 1:20 weight/volume. (3)

CONTRAINDICATIONS

- Severe, unstable or uncontrolled asthma. (4)
- History of any severe systemic or local allergic reaction to an allergen extract. (4)

WARNINGS AND PRECAUTIONS

Severe allergic reactions have occurred following the administration of other allergenic extracts and may occur in individuals following the administration of Non-Standardized Allergenic Extracts in the following situations:

- Extreme sensitivity to Non-Standardized Allergenic Extracts, receipt of high doses of Non-Standardized Allergenic Extracts, or concomitant exposure to similar environmental allergens. (5.1)
- Receiving an accelerated immunotherapy build-up schedule (e.g., “rush” immunotherapy), or changing from one allergenic lot to another. (5.1)

ADVERSE REACTIONS

The most common adverse reactions, occurring in 26 to 82% of all patients who receive subcutaneous immunotherapy, are local adverse reactions at the injection site (e.g., erythema, itching, swelling, tenderness, pain). (6)

Systemic adverse reactions, occurring in ≤ 7% of patients who receive subcutaneous immunotherapy, include generalized skin erythema, urticaria, pruritus, angioedema, rhinitis, wheezing, laryngeal edema, and hypotension. These can be fatal. (6)

To report SUSPECTED ADVERSE REACTIONS, contact GREER Laboratories, Inc. at 1-855-274-1322 or FDA at 1-800-FDA-1088 or www.fda.gov/medwatch.

DRUG INTERACTIONS

- Antihistamines and other medications that suppress histamine, including topical corticosteroids, topical anesthetics and tricyclic antidepressants can interfere with skin test results. (7)

See 17 for PATIENT COUNSELING INFORMATION

FULL PRESCRIBING INFORMATION

WARNING: SEVERE ALLERGIC REACTIONS

- Non-Standardized Allergenic Extracts can cause severe life-threatening systemic reactions, including anaphylaxis. (5.1)
- Do not administer these products to patients with severe, unstable, or uncontrolled asthma. (4)
- Observe patients in the office for at least 30 minutes following treatment. Emergency measures and personnel trained in their use must be available immediately in the event of a life-threatening reaction. (5.1)
- Patients with extreme sensitivity to these products, those on an accelerated immunotherapy build-up schedule, those switching to another allergenic lot, those receiving high doses of Non-Standardized Allergenic Extracts, or those also exposed to similar allergens may be at increased risk of a severe allergic reaction. (5.1)
- These products may not be suitable for patients with certain underlying medical conditions that may reduce their ability to survive a serious allergic reaction. (5.1)
- These products may not be suitable for patients who may be unresponsive to epinephrine or inhaled bronchodilators, such as those taking beta-blockers. (5.2)

1 INDICATIONS AND USAGE

Non-Standardized Allergenic Extracts are indicated for:

- Skin test diagnosis of patients with a clinical history of allergies to one or more of the specific non-standardized allergens.
- Immunotherapy for the reduction of allergen-induced allergic symptoms confirmed by appropriate positive skin tests or by in vitro testing for allergen-specific IgE antibodies.

Food extracts have not been proven safe or effective in allergen immunotherapy.

2 DOSAGE AND ADMINISTRATION

For percutaneous, intradermal or subcutaneous use only.

The extracts are diluted with sterile diluents when used for intradermal testing or subcutaneous immunotherapy. For percutaneous testing, the extracts are diluted with sterile diluents in patients expected to be at greater risk for systemic allergic reaction. Dosages vary by mode of administration and by individual response.

2.1 Preparation for Administration

Parenteral drug products should be inspected visually for particulate matter and discoloration prior to administration, whenever solution and container permit. Discard solution if either of these conditions exist.

The extracts are diluted with sterile diluents when used for percutaneous and intradermal testing, or for subcutaneous immunotherapy.

Extracts labeled “For Diagnostic Use Only” are intended for percutaneous and intradermal testing only. These extracts have not been shown by adequate data to be safe and effective for therapeutic use. The extracts labeled For Diagnostic Use Only are the foods Barley, Coffee, Oat, Pineapple, Rye, Spinach, Wheat, the insects Flea, House Fly, Mosquito, and the plant and plant parts Cottonseed and Flax.

Undiluted 50% glycerin stock concentrate is used for percutaneous testing. To prepare 10-fold dilutions for percutaneous testing in patients suspected to be at greater risk for systemic allergic reaction, start with the stock concentrate. Proceed as shown in Table 1. The 10-fold dilution series uses 0.5 milliliters of concentrate added to 4.5 milliliters of sterile 50% glycerin diluent. Subsequent dilutions are made in a similar manner.

To prepare 10-fold dilutions for intradermal testing and immunotherapy, start with a 1:10 weight/volume, 1:20 weight/volume, or up to a 40,000 PNU/milliliter stock concentrate. Proceed as shown in Table 1. The 10-fold dilution series uses 0.5 milliliter of concentrate added to 4.5 milliliters of sterile diluent (glycerin-free diluents for intradermal testing, glycerin-free or 10% glycerin-saline diluents for immunotherapy). Subsequent dilutions are made in a similar manner.

Table 1: 10-fold Dilution Series*
Dilution | Extract | Milliliters of Diluent | Dilution Strength (w/v) | Dilution Strength (w/v) | Dilution Strength (PNU/milliliter)
0 | Concentrate |  | 1:10 | 1:20 | 20,000
1 | 0.5 mL Concentrate | 4.5 | 1:100 | 1:200 | 2,000
2 | 0.5 mL Dilution 1 | 4.5 | 1:1,000 | 1:2,000 | 200
3 | 0.5 mL Dilution 2 | 4.5 | 1:10,000 | 1:20,000 | 20
4 | 0.5 mL Dilution 3 | 4.5 | 1:100,000 | 1:200,000 | 2
5 | 0.5 mL Dilution 4 | 4.5 | 1:1,000,000 | 1:2,000,000 | 0.2
6 | 0.5 mL Dilution 5 | 4.5 | 1:10,000,000 | 1:20,000,000 | 0.02

*There is no direct potency correlation across the table between PNU/milliliter and w/v.

Undiluted 50% glycerin stock concentrate is used for percutaneous testing. To prepare 5-fold dilutions for percutaneous testing in patients suspected to be at greater risk for systemic allergic reaction, start with the stock concentrate. Proceed as shown in Table 2. The 5-fold dilution series uses 1 milliliter of concentrate added to 4 milliliters of sterile 50% glycerin diluent. Subsequent dilutions are made in a similar manner.

To prepare 5-fold dilutions for intradermal testing or immunotherapy, start with a 1:10 weight/volume, 1:20 weight/volume, or up to a 40,000 PNU/milliliter stock concentrate. Proceed as shown in Table 2. The 5-fold dilution series uses 1 milliliter of concentrate added to 4 milliliters of sterile diluent (glycerin-free diluents for intradermal testing, glycerin-free or 10% glycerin-saline diluents for immunotherapy). Subsequent dilutions are made in a similar manner.

Table 2: 5-fold Dilution Series*
Dilution | Extract | Milliliters of Diluent | Diluent Strength (w/v) | Dilution Strength (w/v) | Dilution Strength (PNU/milliliter)
0 | Concentrate |  | 1:10 | 1:20 | 20,000
1 | 1 mL Concentrate | 4 | 1:50 | 1:100 | 4,000
2 | 1 mL Dilution 1 | 4 | 1:250 | 1:500 | 800
3 | 1 mL Dilution 2 | 4 | 1:1,250 | 1:2,500 | 160
4 | 1 mL Dilution 3 | 4 | 1:6,250 | 1:12,500 | 32
5 | 1 mL Dilution 4 | 4 | 1:31,250 | 1:62,500 | 6.4
6 | 1 mL Dilution 5 | 4 | 1:156,250 | 1:312,500 | 1.28

*There is no direct potency correlation across the table between PNU/milliliter and w/v.

2.2 Diagnostic Testing

Diagnostic testing can be performed via percutaneous or intradermal administration of the Non-Standardized Allergenic Extracts. A positive skin test reaction should be interpreted in relation to the patient’s history and known exposure to the specific allergen(s).

Percutaneous Skin Testing

Preparation and Dose

For percutaneous testing (prick or puncture), use glycerinated extract; use the extracts at the highest available stock concentration. In patients suspected to be at greater risk for systemic allergic reaction, use 10-fold or 5-fold dilutions of the concentrate.

Prick test: Place one drop of extract with appropriate controls on the skin and with a skin test device, pierce through the drop into the skin with a slight lifting motion. Alternatively, use skin test devices loaded with the extract from the storage trays in a similar manner or in accordance with the device manufacturer’s recommendations.

Puncture test: Place one drop of extract or control on the skin and pierce the skin through the drop with a skin test device perpendicular to the skin. Alternatively, use skin test devices loaded with the extract from the storage trays in a similar manner or in accordance with the device manufacturer’s recommendations.

Interpreting Results

When using percutaneous skin test devices, follow the directions provided with the test devices. A glycerinated histamine control solution (6 milligrams/milliliter or 1 milligram/milliliter histamine base) may be used as the positive control. A 50% glycerin-saline solution may be used as the negative control.

Read and record skin test responses 15 to 20 minutes after exposure. Individual patient reactivity can vary with time, allergen potency, and/or immunotherapy, as well as testing technique. The most reliable method of recording a skin test reaction is to measure the largest diameter of both wheal and erythema. While some correlation exists between the size of the skin test reaction and the degree of sensitivity, other factors should be considered in the diagnosis of allergy to specific allergens (see Figure 1 below).

Figure 1: Measurement of Wheal and Flare

Use a paper or plastic millimeter skin reaction guide as shown below.

Fifteen minutes after application of the skin test, measure the length and midpoint orthogonal width of each flare and wheal from the inner edge of the reaction.

The length of the skin test is defined as the largest diameter and the width of the skin test is defined as the diameter perpendicular to the length at its midpoint. Consider the wheal and flare as separate entities. First, measure the flare and then independently measure the wheal.

Measuring the Flare

Measuring the Wheal

The average diameter measurement in the example above of the flare is 26 mm + 36 mm/ 2 = 31 mm and the average diameter of the wheal is 10 mm + 16 mm/2 = 13 mm.

Responses to positive controls should be at least 3 millimeters larger than responses to the negative controls.

Negative controls should elicit no reaction or only reactions of small diameter (less than 2 millimeters wheal, less than 5 millimeters erythema).

If either the positive or negative control response does not meet the above criteria, results for the allergenic extracts tested at the same time should be considered invalid and be repeated.

Intradermal Skin Testing

Preparation and Dose

For intradermal testing, dilute stock concentrate to 1:100 to 1:1000 volume to volume of Non-Standardized Allergenic Extracts stock concentrate solution. Dilute the stock concentrate solution with sterile diluent [see Dosage and Administration (2.1)]. Use normal or buffered saline or normal saline with human serum albumin (HSA) diluent. If the result from the initial test dose is negative, subsequent intradermal tests using increasingly stronger doses may be performed up to the maximum recommended strength of 1:25 volume to volume dilution of the extract concentrate solution.

Inject 0.02 milliliters of the extract solution intradermally according to the algorithms shown in Figure 2.

Figure 2: Algorithm for Dilution of Stock Concentrate Solution of Non-Standardized Allergenic Extracts for Intradermal Skin Testing

^1 Corresponds to 1:10,000 - 1:15,625 volume to volume dilution of 1:20 weight/volume glycerinated extract concentrates

^2 Corresponds to 1:100 - 1:125 volume to volume dilution of 1:20 weight/volume glycerinated extract concentrates

^3 Corresponds to 1:50 - 1:100 volume to volume dilution of 1:20 weight/volume glycerinated extract concentrates

^4 Corresponds to 1:25 - 1:100 volume to volume dilution of 1:20 weight/volume glycerinated extract concentrates

2.3 Immunotherapy

For subcutaneous administration only.

Preparation and Dose

Stock concentrates of Non-Standardized Allergenic Extracts are available in aqueous (up to 1:10 weight/volume or 40,000 PNU/milliliter) and 50% glycerin (up to 1:20 weight/volume) strengths for immunotherapy. Stock concentrates are diluted in normal saline, buffered saline, HSA-saline, or 10% glycerin-saline, depending on the patient’s reactivity to the diluent. See Table 1 and Table 2 for dilution preparation.

Administration of Immunotherapy

Administer immunotherapy by subcutaneous injection in the lateral aspect of the upper arm or thigh. Avoid injection directly into any blood vessel.

The optimal interval between doses of allergenic extract varies among individuals. Injections are usually given 1 to 2 times per week until the maintenance dose is reached, at which time the injection interval is increased to 2, then 3, and finally 4 weeks. Dosages vary by mode of administration, and by clinical response and tolerance. The minimum course of treatment may be three to five years, depending on the clinical response.

Guidelines for Immunotherapy

The initial dose of the extract should be based on the skin test reactivity. In patients suspected to be at greater risk for systemic allergic reaction by history and skin test, the initial dose of the extract should be 0.05 milliliter of a 1:20,000,000 to 1:2,000,000 weight/volume extract dilution. Patients not suspected to be at greater risk for systemic allergic reaction may be started at 0.1 milliliter of a 1:200,000 to 1:20,000 weight/volume extract dilution.

The dose of allergenic extract is increased at each injection by no more than 50% of the previous dose, and the next increment is governed by the response to the last injection.

Select the maximum tolerated maintenance dose based on the patient’s clinical response and tolerance. Doses larger than 0.2 milliliter of the stock concentrate are rarely administered because an extract in 50% glycerin diluent can cause discomfort upon injection.

Dosage Modification Guidelines for Immunotherapy

The following conditions may indicate a need to withhold or reduce the dosage of immunotherapy.

- Symptoms of rhinitis and/or asthma
- Infection accompanied by fever
- Exposure to excessive amounts of clinically relevant environmental allergen prior to a scheduled injection
- Large local reactions that persist for longer than 24 hours can be an indication for repeating the previous dose or reducing the dose at the next administration

Any evidence of a systemic reaction is an indication for a significant reduction (at least 75%) in the subsequent dose. Repeated systemic adverse reactions are sufficient reason for the cessation of further attempts to increase the dose.

Local adverse reactions require a decrease in the next dose by at least 50%. Proceed cautiously in subsequent dosing. In situations prompting dose reduction, once the reduced dose is tolerated, a cautious increase in dosage can be attempted.

Changing extract to a different lot or from a different manufacturer: When switching to a different lot of extract, or from another manufacturer’s extract, decrease the starting dose. Because manufacturing processes and sources of raw materials differ among manufacturers, the interchangeability of extracts from different manufacturers cannot be assured. In general, a dose reduction of 50 to 75% of the previous dose should be adequate, but each situation must be evaluated separately, considering the patient’s history of sensitivity, tolerance of previous injections, and other factors. Dose intervals should not exceed one week when rebuilding the dose.

Unscheduled gaps between treatments: Patients can lose tolerance to allergen injections during prolonged periods between doses, which increases their risk for an adverse reaction. The duration of tolerance between injections varies from patient to patient.

During the build-up phase, when patients receive injections 1 to 2 times per week, repeat or reduce the extract dosage if there has been a substantial time interval between injections. This depends on: 1) the concentration of allergen immunotherapy extract that is to be administered; 2) a previous history of systemic reactions; and 3) the degree of variation from the prescribed interval of time, with longer intervals since the last injection leading to greater reductions in the dose to be administered.

This suggested approach to dose modification, due to unscheduled gaps between treatments during the build-up phase, is not based on published evidence. The individual physician should use this or a similar protocol for the specific clinical setting.

Similarly, if unscheduled gaps occur during maintenance therapy, it may be necessary to reduce the dosage and bring the patient up to maintenance dosing using an established build-up protocol.

Changing from non-stabilized to human serum albumin (HSA) stabilized diluents: Allergenic extracts prepared with diluents containing HSA and 0.4% phenol are more stable than those prepared with diluents that do not contain stabilizers. When switching from a non-stabilized to an HSA-stabilized diluent, consider lowering the dose for immunotherapy.

3 DOSAGE FORMS AND STRENGTHS

Non-Standardized Allergenic Extracts are labeled in weight/volume and/or protein nitrogen units (PNU)/milliliter (a measure of total protein), and are supplied as sterile aqueous stock concentrates at up to 1:10 weight/volume or 40,000 PNU/milliliter, or 50% glycerin stock concentrates at up to 1:20 weight/volume.

4 CONTRAINDICATIONS

Non-Standardized Allergenic Extracts are contraindicated in patients with:

- Severe, unstable or uncontrolled asthma
- History of any severe systemic or local allergic reaction to an allergen extract

5 WARNINGS AND PRECAUTIONS

5.1 Serious Systemic Adverse Reactions

Serious systemic adverse reactions have occurred following the administration of other allergenic extracts and may occur in individuals following the administration of Non-Standardized Allergenic Extracts in the following situations:

- Extreme sensitivity to the specific allergen(s)
- Receipt of an accelerated immunotherapy build-up schedule (e.g., “rush” immunotherapy)
- Receipt of high doses of allergenic extracts or concomitant exposure to similar environmental allergens
- Change from one allergenic extract lot to another allergenic extract lot

High-risk patients have had fatal reactions. Consider using more dilute preparations in patients suspected to be at greater risk of systemic allergic reaction [see Dosage and Administration (2.1)].

Administer Non-Standardized Allergenic Extracts in a healthcare setting under the supervision of a physician prepared to manage a severe systemic or a severe local allergic reaction. Observe patients in the office for at least 30 minutes following administration.^1

5.2 Epinephrine

Non-Standardized Allergenic Extracts may not be suitable for patients with certain medical conditions that may reduce the ability to survive a serious allergic reaction or increase the risk of adverse reactions after epinephrine administration. Examples of these medical conditions include but are not limited to: markedly compromised lung function (either chronic or acute), unstable angina, recent myocardial infarction, significant arrhythmia, and uncontrolled hypertension.

These products may not be suitable for patients who are taking medications that can potentiate or inhibit the effect of epinephrine. These medications include:

Βeta-adrenergic blockers: Patients taking beta-adrenergic blockers may be unresponsive to the usual doses of epinephrine used to treat serious systemic reactions, including anaphylaxis. Specifically, beta-adrenergic blockers antagonize the cardiostimulating and bronchodilating effects of epinephrine.

Alpha-adrenergic blockers, ergot alkaloids: Patients taking alpha-adrenergic blockers may be unresponsive to the usual doses of epinephrine used to treat serious systemic reactions, including anaphylaxis. Specifically, alpha-adrenergic blockers antagonize the vasoconstricting and hypertensive effects of epinephrine. Similarly, ergot alkaloids may reverse the pressor effects of epinephrine.

Tricyclic antidepressants, levothyroxine sodium, monoamine oxidase inhibitors, and certain antihistamines: The adverse effects of epinephrine may be potentiated in patients taking tricyclic antidepressants, levothyroxine sodium, monoamine oxidase inhibitors, and the antihistamines chlorpheniramine, and diphenhydramine.

Cardiac glycosides, diuretics: Patients who receive epinephrine while taking cardiac glycosides or diuretics should be observed carefully for the development of cardiac arrhythmias.

5.3 Anaphylaxis Following False Negative Food Allergen Skin Test Results
False negative skin test results associated with anaphylaxis from subsequent exposure to the allergen have been reported during postmarketing diagnostic use of some food allergenic extracts. Based on the patient’s clinical history and index of suspicion, healthcare providers should consider confirming negative skin testing with serologic testing by measuring specific serum IgE or with a medically-supervised oral food challenge.

5.4 Cross-Reactions and Dose Sensitivity

When determining the final dose of an allergen mixture for immunotherapy, consider cross-reactivity among component extracts.

Determine the initial dilution of allergenic extract, starting dose, and progression of dosage based on the patient’s history and results of skin tests^2 [see Dosage and Administration (2.1)]. Strongly positive skin tests can be indicators for potential adverse reactions.

6 ADVERSE REACTIONS

The most common adverse reactions, occurring in 26 to 82% of all patients who receive subcutaneous immunotherapy are local adverse reactions at the injection site (e.g., erythema, itching, swelling, tenderness, pain).^1 Systemic adverse reactions, occurring in < 7% of patients who receive subcutaneous immunotherapy,^3 include generalized skin erythema, urticaria, pruritus, angioedema, rhinitis, wheezing, laryngeal edema, and hypotension. These adverse reactions can be fatal.^1

The allergenic extracts labeled “For Diagnostic Use Only” that contain sodium formaldehyde sulfoxylate (SFS) can cause slight discoloration of the skin at the site of administration. This discoloration can remain for extended amounts of time.

7 DRUG INTERACTIONS

7.1 Antihistamines

Do not perform skin testing with allergenic extracts within 3 to 10 days of use of first-generation H1-histamine receptor blockers (e.g., clemastine, diphenhydramine) and second-generation antihistamines (e.g., loratadine, cetirizine). These products suppress histamine skin test reactions and could mask a positive response.^2

7.2 Topical Corticosteroids and Topical Anesthetics

Topical corticosteroids can suppress skin reactivity; therefore, discontinue use at the skin test site for 2 to 3 weeks before skin testing. Avoid use of topical local anesthetics at skin test sites as they can suppress flare responses.^2

7.3 Tricyclic Antidepressants

Tricyclic antidepressants can have potent antihistamine effects that can affect skin testing. If tricyclic medication has been recently discontinued, allow 7 to 14 days before initiating skin testing.^2

8 USE IN SPECIFIC POPULATIONS

8.1 Pregnancy

Risk Summary

All pregnancies have a risk of birth defect, loss, or other adverse outcomes. In the U.S. general population, the estimated background risk of major birth defects and miscarriage in clinically recognized pregnancies is 2 to 4% and 15 to 20%, respectively. There are no human or animal data to establish the presence or absence of Non-Standardized Allergenic Extracts-associated risks during pregnancy.

8.2 Lactation

Risk Summary

It is not known whether Non-Standardized Allergenic Extracts are present in human milk. Data are not available to assess the effects of these extracts on the breastfed child or on milk production/excretion. The developmental and health benefits of breastfeeding should be considered along with the mother’s clinical need for Non-Standardized Allergenic Extracts and any potential adverse effects on the breastfed child from the extracts or from the underlying maternal condition.

8.4 Pediatric Use

For use of these products in children younger than 5 years of age, consideration should be given to the patient’s ability to comply and cooperate with allergen immunotherapy and the potential for difficulty in communicating with the child regarding systemic reactions.^1

8.5 Geriatric Use

Data are not available to determine if subjects 65 years of age and older respond differently to allergen immunotherapy than younger subjects.

11 DESCRIPTION

Non-Standardized Allergenic Extracts are sterile solutions used for percutaneous testing, intradermal testing, or subcutaneous immunotherapy. Aqueous extracts contain the soluble extractants of the source material in water for injection, 0.5% sodium chloride, 0.54% sodium bicarbonate, and 0.4% phenol. Glycerinated extracts contain the soluable extractants of the source material in water for injection and 50% glycerin, 0.25% sodium chloride, 0.27% sodium bicarbonate, and 0.2% phenol. The pH of the extracts range from 6 to 9.

Certain food extracts (Barley, Oat, Pineapple, Rye, Spinach, and Wheat), labeled “For Diagnostic Use Only”, contain 0.1% sodium formaldehyde sulfoxylate as an antioxidant.

Source materials used in the manufacture of allergenic extracts are collected from natural sources or from laboratory cultures.

Non-Standardized Allergenic Extracts appear as clear and colorless to dark brown solutions that should be free of particulate matter.

Extracts are labeled either as weight-to-volume based on the weight of the source material to the volume of the extracting fluid, or as PNU/milliliter with one PNU representing 0.00001 mg of protein nitrogen per milliliter.

12 CLINICAL PHARMACOLOGY

12.1 Mechanism of Action

The skin test reaction results from interaction of the introduced allergen and allergen-specific IgE antibodies bound to mast cells, leading to mast cell degranulation and release of histamine, tryptase and other mediators, which results in the formation of the wheal and flare.

The precise mechanisms of action of allergen immunotherapy are not known. Immunologic responses to immunotherapy include changes in allergen-specific IgE levels, allergen-specific IgG levels, and regulatory T cell responses.^1

14 CLINICAL STUDIES

Specific immunotherapy with allergenic extracts is helpful in reducing symptoms associated with exposure to the offending allergens. A summary of effectiveness by the Panel on Review of Allergenic Extracts, an advisory committee to the U.S. Food and Drug Administration, has been published.^4

15 REFERENCES

1. Cox LJ, Nelson H, Lockey R. Allergen immunotherapy: A practice parameter third update. J Allergy Clin Immunol. 2011;127:(1)S1-55.
2. Bernstein IL, Li JT, Bernstein DI, et al. Allergy diagnostic testing: an updated practice parameter. Ann Allergy Asthma Immunol. 2008;100:S1-148.
3. Greenberg MA, Kaufman CR, Gonzalez GE, et al. Late and immediate systemic-allergic reactions to inhalant allergen immunotherapy. J Allergy Clin Immunol. 1986;77:865-870.
4. Federal Register Proposed Rule: Biological Products: Implementation of Efficacy Review, Allergenic Extracts, Federal Register 1985;50: 3082-3288.

16 HOW SUPPLIED/STORAGE AND HANDLING

Non-Standardized Allergenic Extracts and mixes may be supplied as aqueous stock concentrates of up to 1:10 weight/volume or 40,000 PNU/milliliter for intradermal and subcutaneous testing. The extracts may also be supplied as 50% glycerin stock concentrates of up to 1:20 weight/volume for use in percutaneous skin testing and subcutaneous immunotherapy. Non-Standardized Allergenic Extracts are labeled in weight/volume and/or PNU/milliliter and may be provided in 5, 10, and 50 milliliter vials. Glycerinated extracts are also supplied in 5 milliliter dropper vials for prick or puncture testing.

Non-Standardized Allergenic Extracts available are as follows:

Pollens ‑ Grasses

Bahia Grass, Paspalum notatum

Brome, Smooth, Bromus inermis

Canarygrass, Reed, Phalaris arundinacea

Johnson Grass, Sorghum halepense

Quack (Couch) Grass, Elymus repens

Ryegrass, Giant Wild, Leymus condensatus

Ryegrass, Italian, Lolium multiflorum

Velvetgrass, Holcus lanatus

Wheatgrass, Western, Pascopyrum smithii

Pollens - Trees

Acacia, Acacia dealbata

Alder, Hazel, Alnus serrulata

Alder, Red, Alnus rubra

Alder, White, Alnus rhombifolia

Ash, Arizona (Velvet), Fraxinus velutina

Ash, Green, Fraxinus pennsylvanica

Ash Mix (Equal parts Fraxinus pennsylvanica, Fraxinus americana)

Ash, Oregon, Fraxinus latifolia

Ash, White, Fraxinus americana

Aspen, Populus tremuloides

Beech, American, Fagus grandifolia

Birch, Black-Sweet, Betula lenta

Birch, Mix (Equal parts Betula lenta, Betula nigra, Betula populifolia)

Birch, River, Betula nigra

Birch, Spring, Betula occidentalis

Birch, White, Betula populifolia

Box Elder, Acer negundo

Cedar, Mountain, Juniperus ashei

Cedar, Red, Juniperus virginiana

Cedar, Salt (Tamarisk), Tamarix gallica

Central/Eastern 4 Tree Mix (Equal parts Ulmus americana, Acer negundo, Carya illinoinensis, Quercus virginiana)

Cottonwood, Arizona (Fremont), Populus fremontii

Cottonwood, Black, Populus trichocarpa

Cottonwood, Eastern, Populus deltoides

Cottonwood, Western, Populus deltoides ssp. monilifera

Cypress, Arizona, Callitropsis arizonica

Cypress, Bald, Taxodium distichum

Eastern Oak Mix (Equal parts Quercus velutina, Quercus rubra, Quercus alba)

Eastern 6 Tree Mix (Equal parts Fagus grandifolia, Populus deltoides, Quercus rubra, Betula nigra, Carya ovata, Fraxinus americana)

Eastern 7 Tree Mix (Equal parts Ulmus americana, Fagus grandifolia, Populus deltoides, Quercus rubra, Betula nigra, Carya ovata, Fraxinus americana)

Eastern 8 Tree Mix (Equal parts Ulmus americana, Fagus grandifolia, Populus deltoides, Quercus rubra, Betula nigra, Carya ovata, Fraxinus americana, Acer saccharum)

Eastern 10 Tree Mix (Equal parts Platanus occidentalis, Ulmus americana, Fagus grandifolia, Populus deltoides, Quercus rubra, Betula nigra, Carya ovata, Fraxinus americana, Acer saccharum, Liquidambar styraciflua)

Elm, American, Ulmus americana

Elm, Cedar, Ulmus crassifolia

Elm Mix (Equal parts Ulmus americana, Ulmus pumila)

Elm, Siberian, Ulmus pumila

Eucalyptus, Bluegum, Eucalyptus globulus

Hackberry, Celtis occidentalis

Hazelnut, American, Corylus americana

Hickory Mix (Equal parts Carya glabra, Carya ovata, Carya laciniosa, Carya tomentosa)

Hickory-Pecan Mix (Equal parts Carya illinoinensis, Carya ovata)

Hickory, Shagbark, Carya ovata

Hickory, Shellbark, Carya laciniosa

Hickory, White, Carya tomentosa

Juniper Mix (Equal parts Juniperus monosperma, Juniperus scopulorum)

Juniper, Oneseed, Juniperus monosperma

Juniper, Pinchot, Juniperus pinchotii

Juniper, Rocky Mountain, Juniperus scopulorum

Juniper, Utah, Juniperus osteosperma

Juniper, Western, Juniperus occidentalis

Locust Blossom, Black, Robinia pseudoacacia

Mango Blossom, Mangifera indica

Maple-Box Elder Mix (Equal parts Acer saccharum, Acer negundo)

2 Maple Mix (Equal parts Acer rubrum, Acer saccharum)

3 Maple Mix (Equal parts Acer rubrum, Acer saccharinum, Acer saccharum)

Maple, Red, Acer rubrum

Maple, Silver/Soft, Acer saccharinum

Maple, Sugar/Hard, Acer saccharum

Melaleuca, Melaleuca quinquenervia

Mesquite, Velvet Prosopis velutina

Mulberry, Paper, Broussonetia papyrifera

Mulberry, Red, Morus rubra

Mulberry, White, Morus alba

Oak, Arizona (Gambel), Quercus gambelii

Oak, Black, Quercus velutina

Oak, Bur, Quercus macrocarpa

Oak, California Black, Quercus kelloggii

Oak, California Live, Quercus agrifolia

Oak, California White, Quercus lobata

Oak, Post, Quercus stellata

Oak, Red, Quercus rubra

Oak, Virginia Live, Quercus virginiana

Oak, Water, Quercus nigra

Oak, Western White, Quercus garryana

Oak, White, Quercus alba

Olive, Olea europaea

Olive, Russian, Elaeagnus angustifolia

Orange Pollen, Citrus X sinensis

Palm, Queen, Syagrus romanzoffiana

Pecan, Carya illinoinensis

Peppertree Mix (Equal parts Schinus molle, Schinus terebinthifolius)

Pine, Australian (Beefwood), Casuarina equisetifolia

Pine, Loblolly, Pinus taeda

Pine, Longleaf, Pinus palustris

Pine Mix (Equal parts Pinus taeda, Pinus strobus, Pinus echinata)

Pine, Ponderosa, Pinus ponderosa

Pine, Virginia Scrub, Pinus virginiana

Pine, White (Eastern), Pinus strobus

Pine, White (Western), Pinus monticola

Pine, Yellow, Pinus echinata

Poplar, Lombardy’s, Populus nigra

Poplar, White, Populus alba

Privet, Ligustrum vulgare

Sweetgum, Liquidambar styraciflua

Sycamore, American, Platanus occidentalis

Sycamore, California (Western), Platanus racemosa

11 Tree Mix (Equal parts Fagus grandifolia, Platanus occidentalis, Ulmus americana, Juglans nigra, Salix nigra, Populus deltoides, Quercus rubra, Betula nigra, Carya ovata, Acer saccharum, Fraxinus americana)

Walnut, Black, Juglans nigra

Walnut, California Black, Juglans californica

Walnut, English, Juglans regia

Wax Myrtle, Morella cerifera

Western Oak Mix (Equal parts Quercus kelloggii, Quercus agrifolia, Quercus garryana)

Western 3 Tree Mix (Equal parts Olea europaea, Ulmus pumila, Platanus racemosa)

Western 10 Tree Mix (Equal parts Acacia dealbata, Acer negundo, Populus fremontii, Olea europaea, Ulmus pumila, Betula occidentalis, Juniperus occidentalis, Platanus racemosa, Quercus garryana, Morus alba)

Western Walnut Mix (Equal parts Juglans californica, Juglans regia)

Willow, Arroyo, Salix lasiolepis

Willow, Black, Salix nigra

Pollens - Weeds and Garden Plants

Allscale, Atriplex polycarpa

Amaranth, Green, Amaranthus hybridus

Baccharis Mix (Equal parts Baccharis sarothroides, Baccharis halimifolia)

Burningbush (Kochia), Kochia scoparia spp. scoparia

Burrobrush, Ambrosia salsola

Central/Western Weed Mix (Equal parts Kochia scoparia ssp. scoparia, Chenopodium album, Salsola kali)

Cocklebur, Xanthium strumarium

Common Weed Mix (Equal parts Xanthium strumarium, Plantago lanceolata, Chenopodium album, Amaranthus retroflexus, Salsola kali)

Dock-Sorrel Mix (Equal parts Rumex acetosella, Rumex crispus)

Dock, Yellow (Curly), Rumex crispus

Dogfennel, Eupatorium capillifolium

Goldenrod, Solidago canadensis

Iodinebush, Allenrolfea occidentalis

Lamb's Quarters, Chenopodium album

Lenscale (Quailbrush), Atriplex lentiformis

Marsh Elder, True (Rough), Iva annua

Marshelder, Burweed (Giant Poverty), Cyclachaena xanthiifolia

Mixed Amaranths (Equal parts Amaranthus hybridus, Amaranthus palmeri, Amaranthus retroflexus)

Mugwort, Common, Artemisia vulgaris

National Weed Mix (Equal parts Xanthium strumarium, Ambrosia trifida, Chenopodium album, Amaranthus retroflexus, Ambrosia artemisiifolia)

Nettle, Urtica dioica

Palmer's Amaranth, Amaranthus palmeri

Pigweed, Rough Redroot, Amaranthus retroflexus

Pigweed, Spiny, Amaranthus spinosus

Plantain, English, Plantago lanceolata

Plantain-Sorrel Mix (Equal parts Plantago lanceolata, Rumex acetosella)

Rabbit Bush, Ambrosia deltoidea

Ragweed, Desert, Ambrosia dumosa

Ragweed, False, Ambrosia acanthicarpa

Ragweed, Giant (Tall), Ambrosia trifida

Ragweed, Lanceleaf, Ambrosia bidentata

Ragweed, Slender, Ambrosia confertiflora

Ragweed, Western, Ambrosia psilostachya

Russian Thistle, Salsola kali

Sagebrush, Common, Artemisia tridentata

Sage Mix (Equal parts Artemisia tridentata, Artemisia ludoviciana)

Sage, Prairie, Artemisia ludoviciana

Saltbush, Annual, Atriplex wrightii

Scale/Atriplex Mix (Equal parts Atriplex polycarpa, Atriplex lentiformis, Atriplex canescens)

Sorrel, Sheep (Red), Rumex acetosella

Waterhemp, Tall, Amaranthus tuberculatus

3 Weed Mix (Equal parts Xanthium strumarium, Chenopodium album, Amaranthus retroflexus)

Western Ragweed Mix (Equal parts Ambrosia acanthicarpa, Ambrosia psilostachya)

Wingscale, Atriplex canescens

Plants and Plant Parts

Cotton Linters, Gossypium hirsutum

Cottonseed, Gossypium hirsutum (For Diagnostic Use Only)

Flax, Linum usitatissimum (For Diagnostic Use Only)

Gum, Arabic, Acacia senegal

Gum, Karaya, Sterculia urens

Gum, Tragacanth, Astragalus gummifer

Kapok, Ceiba pentandra

Orris Root, Iris germanica

Pyrethrum, Chrysanthemum cinerariifolium

Tobacco, Cultivated, Leaf, Nicotiana tabacum

Pollens - Cultivated Farm Plants

Alfalfa, Medicago sativa

Beet, Sugar, Beta vulgaris

Corn, Cultivated, Zea mays

Oat, Cultivated, Avena sativa

Rape (Mustard), Brassica napus

Red Clover, Trifolium pratense

Rye, Cultivated, Secale cereale

Wheat, Cultivated, Triticum aestivum

Pollens - Flowers

Daisy, Leucanthemum vulgare

Dandelion, Taraxacum officinale

Sunflower, Helianthus annuus

Molds, Rusts and Smuts

AHH Mold Mix (Equal parts Alternaria alternata, Bipolaris sorokiniana, Cladosporium sphaerospermum)

Alternaria alternata

Alternaria/Hormodendrum Mix (Equal parts Alternaria alternata, Cladosporium sphaerospermum)

Aspergillus amstelodami

Aspergillus flavus

Aspergillus fumigatus

Aspergillus Mix (Equal parts Aspergillus amstelodami, Aspergillus flavus, Aspergillus fumigatus, Aspergillus nidulans, Aspergillus niger)

Aspergillus nidulans

Aspergillus niger

Aureobasidium pullulans

Bermuda Grass Smut, Ustilago cynodontis

Bipolaris sorokiniana

Botrytis cinerea

Candida albicans

Chaetomium globosum

Cladosporium herbarum

Cladosporium sphaerospermum

Corn Smut, Ustilago maydis

Curvularia spicifera

Dematiaceae Mix (Equal parts Alternaria alternata, Aureobasidium pullulans, Bipolaris sorokiniana, Cladosporium herbarum, Curvularia spicifera, Helminthosporium solani)

Epicoccum nigrum

Epidermophyton floccosum

Fusarium Mix (Equal parts Gibberella fujikuroi, Fusarium solani)

Fusarium solani

Geotrichum candidum

Gibberella fujikuroi

Gliocladium viride

Grain Smut Mix (Equal parts Ustilago maydis, Ustilago tritici, Ustilago nuda, Ustilago avenae)

Grass Smut Mix (Equal parts Ustilago cynodontis, Sporisorium cruentum)

Helminthosporium solani

Hypomyces perniciousus

Loose Kernel Smut, Sporisorium cruentum

Loose Smut, Wheat, Ustilago tritici

Microsporum canis

Mold Mix #1 (Equal parts Alternaria alternata, Aspergillus niger, Bipolaris sorokiniana, Cladosporium sphaerospermum, Penicillium chrysogenum var. chrysogenum)

Mold Mix #2 (Equal parts Aureobasidium pullulans, Curvularia spicifera, Gibberella fujikuroi, Mucor plumbeus, Rhizopus stolonifer)

Mold Mix #3 (Equal parts Alternaria alternata, Aspergillus niger, Cladosporium sphaerospermum, Penicillium chrysogenum var. chrysogenum)

Monilia Mix (Equal parts Candida albicans, Neurospora intermedia)

Mucor circinelloides f. circinelloides

Mucor circinelloides f. lusitanicus

Mucor Mix (Equal parts Mucor circinelloides f. lusitanicus, Mucor plumbeus)

Mucor plumbeus

Neurospora intermedia

New Stock Fungi Mix (Equal parts Sarocladium strictum, Alternaria alternata, Aspergillus niger, Aureobasidium pullulans, Bipolaris sorokiniana, Botrytis cinerea, Candida albicans, Chaetomium globosum, Cladosporium sphaerospermum, Epicoccum nigrum, Gibberella fujikuroi, Mucor plumbeus, Penicillium chrysogenum var. chrysogenum, Phoma betae, Rhizopus stolonifer, Trichophyton mentagrophytes)

Oat Smut, Ustilago avenae

Paecilomyces variotii

Penicillium chrysogenum var. chrysogenum

Penicillium digitatum

Penicillium Mix (Equal parts Penicillium camemberti, Penicillium chrysogenum, Penicillium digitatum, Penicillium chrysogenum var. chrysogenum, Penicillium roqueforti)

Phoma betae

Phycomycetes Mix (Equal parts Mucor circinelloides f. lusitanicus, Rhizopus stolonifer)

Rhizopus arrhizus

Rhizopus Mix (Equal parts Rhizopus stolonifer, Rhizopus arrhizus)

Rhizopus stolonifer

Rhodotorula mucilaginosa

Saccharomyces cerevisiae

Sarocladium strictum

Stemphylium solani

Trichoderma harzianum

Trichophyton mentagrophytes

Trichophyton rubrum

Trichothecium roseum

Animal Allergens

Canary Feathers, Serinus canaria

Cattle Epithelia, Bos taurus

Chicken Feathers, Gallus gallus

Dog Epithelia, Canis lupus familiaris

Duck Feathers, Anas platyrhynchos

Gerbil Epithelia, Meriones unguiculatus

Goat Epithelia, Capra hircus

Goose Feathers, Anser anser

Guinea Pig Epithelia, Cavia porcellus

Hamster Epithelia, Mesocricetus auratus

Hog Epithelia, Sus scrofa

Horse Epithelia, Equus caballus

Mixed Feathers (Equal parts Gallus gallus, Anas platyrhynchos, Anser anser)

Mouse Epithelia, Mus musculus

Parakeet Feathers, Melopsittacus undulatus

Rabbit Epithelia, Oryctolagus cuniculus

Rat Epithelia, Rattus norvegicus

Silk Worm Cocoon, Bombyx mori

Insects (Whole Body)

Ant, Black Carpenter, Camponotus pennsylvanicus

Ant, Fire, Solenopsis invicta

Ant, Fire, Solenopsis richteri

Cockroach, American, Periplaneta americana

Cockroach, German, Blattella germanica

2 Cockroach Mix (Equal parts Periplaneta americana, Blattella germanica)

Deer Fly, Chrysops vittatus

Flea, Ctenocephalis felis (For Dagnostic Use Only)

House Fly, Musca domestica (For Dagnostic Use Only)

Mosquito, Aedes taeniorhynchus (For Diagnostic Use Only)

Food - Animal Products and Poultry Products

Beef, Bos taurus

Chicken Meat, Gallus gallus

Egg, White, Chicken, Gallus gallus

Egg, Whole, Chicken, Gallus gallus

Egg, Yolk, Chicken, Gallus gallus

Lamb, Ovis aries

Pork, Sus scrofa

Turkey Meat, Meleagris gallopavo

Food - Dairy Products

Milk, Cow, Bos taurus

Food - Fish and Shellfish

Bass, Black, Centropristis striata

Catfish, Channel, Ictalurus punctatus

Clam, Northern Quahog, Mercenaria mercenaria

Cod, Atlantic, Gadus morhua

Crab, Blue, Callinectes sapidus

Fish Mix (Equal parts Gadus morhua, Paralichthys lethostigma, Hippoglossus hippoglossus, Scomber scombrus, Thunnus albacares)

Flounder, Southern, Paralichthys lethostigma

Lobster, American, Homarus americanus

Mackerel, King/Atlantic, Scomber scombrus

Oyster, Atlantic/Eastern, Crassostrea virginica

Perch, Ocean, Sebastes alutus

Salmon, Atlantic, Salmo salar

Scallops, Sea, Placopecten magellanicus

Shellfish Mix (Equal parts Mercenaria mercenaria, Callinectes sapidus, Crassostrea virginica, Placopecten magellanicus, Farfantepenaeus aztecus)

Shrimp, Brown, Farfantepenaeus aztecus

Trout, Rainbow, Oncorhynchus mykiss

Tuna, Yellowfin, Thunnus albacares

Food - Plant Source

Almond, Prunus dulcis

Apple, Malus pumila

Apricot, Prunus armeniaca

Banana, Musa acuminata

Barley, Whole Grain, Hordeum vulgare (For Diagnostic Use Only, Contains SFS*)

Bean, Lima, Phaseolus lunatus

Bean, Navy, Phaseolus vulgaris

Bean, String Green, Phaseolus vulgaris

Blueberry, Velvetleaf, Vaccinium myrtilloides

Brazil Nut, Bertholletia excelsa

Broccoli, Brassica oleracea var. botrytis

Buckwheat, Fagopyrum esculentum

Cabbage, Brassica oleracea var. capitata

Cacao Bean, Theobroma cacao

Cantaloupe, Cucumis melo

Carrot, Daucus carota

Cashew Nut, Anacardium occidentale

Cauliflower, Brassica oleracea var. botrytis

Celery, Apium graveolens var. dulce

Cherry, Sweet, Prunus avium

Cinnamon, Cinnamomum verum

Coconut, Cocos nucifera

Coffee, Coffea arabica (For Diagnostic Use Only)

Corn, Zea mays

Cranberry, Vaccinium macrocarpon

Cucumber, Cucumis sativus

Garlic, Allium sativum

Ginger, Zingiber officinale

Grape, White Seedless, Vitis vinifera

Grapefruit, Citrus X paradisi

Hazelnut (Filbert), Corylus americana

Hops, Humulus lupulus

Lemon, Citrus X limon

Lettuce, Lactuca sativa

Malt (Barley), Hordeum vulgare

Mushroom, Agaricus campestris

Mustard Seed, Sinapis alba

Nutmeg, Myristica fragrans

Oat, Avena sativa (For Diagnostic Use Only, Contains SFS*)

Olive, Green, Olea europaea

Onion, Allium cepa

Orange, Citrus X sinensis

Pea, Green or English, Pisum sativum

Peach, Prunus persica

Peanut, Arachis hypogaea

Pear, Pyrus communis

Pecan, Carya illinoinensis

Pepper, Black, Piper nigrum

Pepper, Green, Capsicum annuum

Pineapple, Ananas comosus (For Diagnostic Use Only, Contains SFS*)

Potato, Sweet, Ipomoea batatas

Potato, White, Solanum tuberosum

Raspberry, Red, Rubus idaeus

Rice, Oryza sativa

Rye, Secale cereale (For Diagnostic Use Only, Contains SFS*)

Sesame Seed, Sesamum indicum

Soybean, Glycine max

Spinach, Spinacia oleracea (For Diagnostic Use Only, Contains SFS*)

Squash, Yellow Summer, Cucurbita pepo var. ovifera

Strawberry, Fragaria X ananassa

Tomato, Solanum lycopersicum

Vanilla, Vanilla planifolia

Walnut, Black, Juglans nigra

Walnut, English, Juglans regia

Watermelon, Citrullus lanatus

Wheat, Whole, Triticum aestivum (For Diagnostic Use Only, Contains SFS*)

16.2 Storage and Handling

Maintain at 2 to 8°C (36 to 46°F) during storage and use.

Dilutions of concentrated extracts that result in a glycerin content of less than 50% can reduce extract stability. Extract dilutions at 1:100 volume to volume should be kept no longer than a month, and more dilute solutions no more than a week. The potency of a dilution can be checked by skin test comparison to a fresh dilution of the extract on a known allergic patient.

17 PATIENT COUNSELING INFORMATION

Instruct patient to remain under observation in the office for 30 minutes or longer after an injection.

Caution patient that reactions can occur more than 30 minutes after skin testing or an injection.

Instruct patient to recognize the following symptoms as adverse reactions and to immediately return to the office or immediately seek other medical attention if any of these symptoms occur following skin testing or an injection:

- Unusual swelling and/or tenderness at the injection site
- Hives or itching of the skin
- Swelling of the face and/or mouth
- Sneezing, coughing or wheezing
- Shortness of breath
- Nausea
- Dizziness or faintness

Manufacturer:

U.S. License No. 308

GREER Laboratories, Inc.

Lenoir, NC 28645 U.S.A